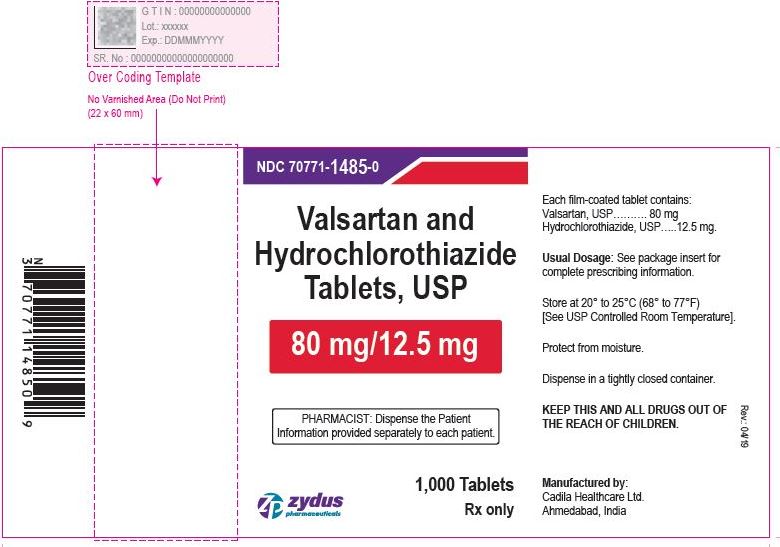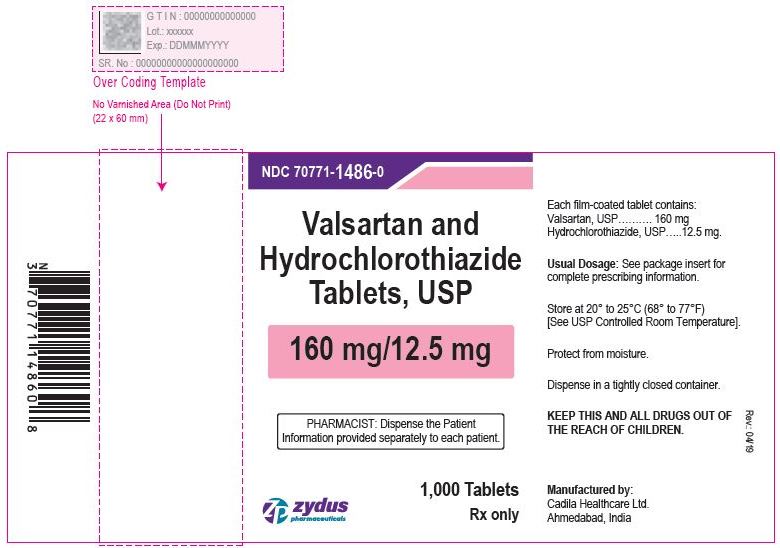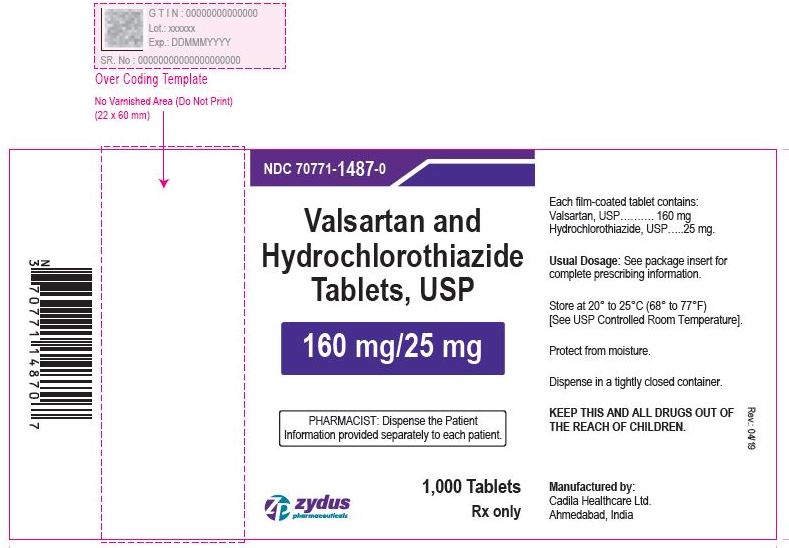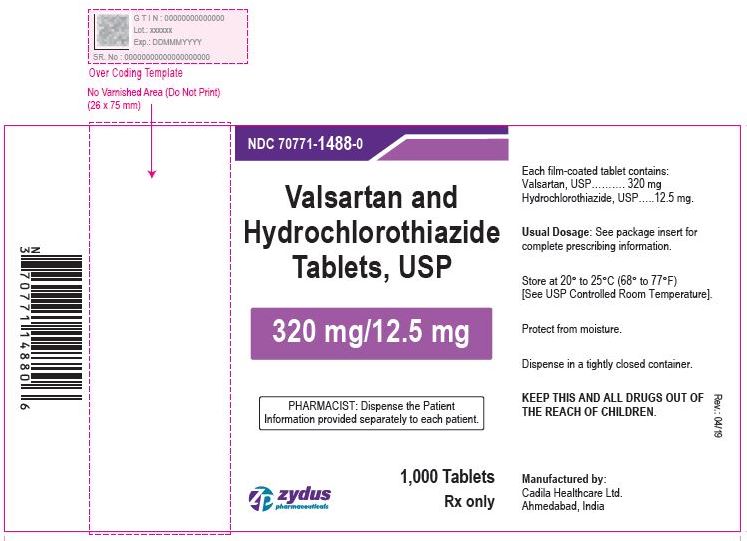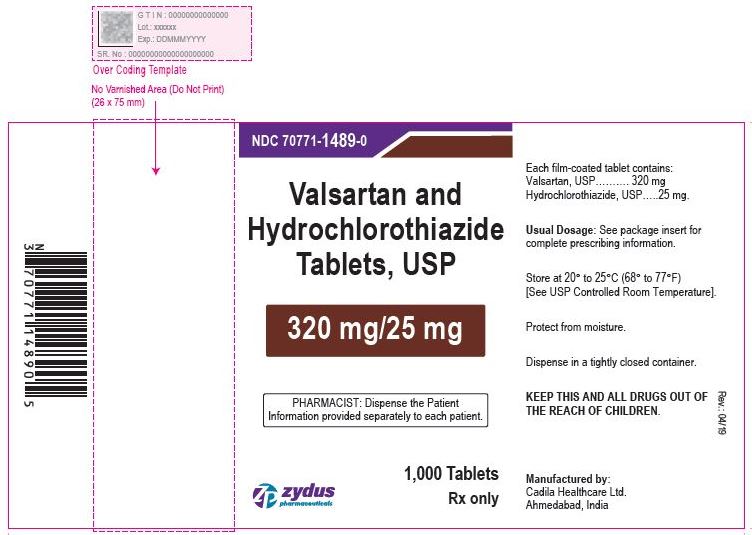 DRUG LABEL: valsartan and hydrochlorothiazide
NDC: 70771-1485 | Form: TABLET, FILM COATED
Manufacturer: Zydus Lifesciences Limited
Category: prescription | Type: HUMAN PRESCRIPTION DRUG LABEL
Date: 20221105

ACTIVE INGREDIENTS: VALSARTAN 80 mg/1 1; HYDROCHLOROTHIAZIDE 12.5 mg/1 1
INACTIVE INGREDIENTS: ANHYDROUS DIBASIC CALCIUM PHOSPHATE; CELLULOSE, MICROCRYSTALLINE; CROSPOVIDONE; FERRIC OXIDE RED; FERRIC OXIDE YELLOW; HYPROMELLOSES; MAGNESIUM STEARATE; POLYETHYLENE GLYCOL 4000; SILICON DIOXIDE; TALC; TITANIUM DIOXIDE

VALSARTAN AND HYDROCHLOROTHIAZIDE TABLETS

PACKAGE LABEL.PRINCIPAL DISPLAY PANEL

Valsartan and Hydrochlorothiazide Tablets USP, 80/12.5 mg

NDC 70771-1485-0 in bottle of 1000 tablets

1000 tablets

Rx only

Valsartan and Hydrochlorothiazide Tablets USP, 160/12.5 mg

NDC 70771-1486-0 in bottle of 1000 tablets

1000 tablets

Rx only

Valsartan and Hydrochlorothiazide Tablets USP, 160/25 mg

NDC 70771-1487-0 in bottle of 1000 tablets

1000 tablets

Rx only

Valsartan and Hydrochlorothiazide Tablets USP, 320/12.5 mg

NDC 70771-1488-0 in bottle of 1000 tablets

1000 tablets

Rx only

Valsartan and Hydrochlorothiazide Tablets USP, 320/25 mg

NDC 70771-1489-0 in bottle of 1000 tablets

1000 tablets

Rx only